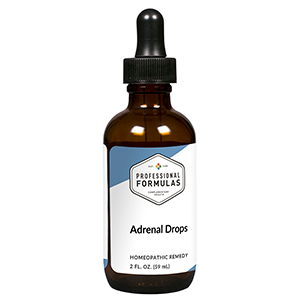 DRUG LABEL: Adrenal Drops
NDC: 63083-5001 | Form: LIQUID
Manufacturer: Professional Complementary Health Formulas
Category: homeopathic | Type: HUMAN OTC DRUG LABEL
Date: 20190815

ACTIVE INGREDIENTS: MILK THISTLE 2 [hp_X]/59 mL; GINGER 2 [hp_X]/59 mL; ECHINACEA PURPUREA WHOLE 2 [hp_X]/59 mL; BERBERIS VULGARIS ROOT BARK 3 [hp_X]/59 mL; CHELIDONIUM MAJUS WHOLE 3 [hp_X]/59 mL; BRYONIA ALBA ROOT 4 [hp_X]/59 mL; SUS SCROFA ADRENAL GLAND 6 [hp_X]/59 mL; BOS TAURUS SPLEEN 6 [hp_X]/59 mL; ATROPINE SULFATE 6 [hp_X]/59 mL; MAGNESIUM PHOSPHATE, DIBASIC TRIHYDRATE 8 [hp_X]/59 mL; SILVER NITRATE 9 [hp_X]/59 mL; LYCOPODIUM CLAVATUM SPORE 12 [hp_X]/59 mL
INACTIVE INGREDIENTS: ALCOHOL; WATER

HAD

ACTIVE INGREDIENTS

Carduus marianus 2X
Zingiber officinale 2X
Echinacea purpurea 2X
Berberis vulgaris 3X
Chelidonium majus 3X
Bryonia 4X
Adrenal 6X, 12X
Spleen 6X
Atropinum sulphuricum 6X
Magnesia phosphorica 8X
Argentum nitricum 9X
Lycopodium clavatum 12X

QUESTIONS

Professional Formulas

PO Box 2034 Lake Oswego, OR 97035

INDICATIONS

For the temporary relief of lethargy, lack of energy, sadness, anxiousness, or decreased ability to handle stress.*

PURPOSE

*Claims based on traditional homeopathic practice, not accepted medical evidence. Not FDA evaluated.

WARNINGS

In case of overdose, get medical help or contact a poison control center right away.

Keep out of the reach of children.

PREGNANCY OR BREAST FEEDING

If pregnant or breastfeeding, ask a healthcare professional before use.

DIRECTIONS

Place drops under tongue 30 minutes before/after meals. Adults and children 12 years and over: Take 10 drops up to 3 times per day. Consult a physician for use in children under 12 years of age.

OTHER INFORMATION

Tamper resistant. If seal is broken, do not use. After opening, close container tightly and store at room temperature away from heat.

INACTIVE INGREDIENTS

20% ethanol, purified water.

LABEL

Est 1985

Professional Formulas

Complementary Health

Adrenal Drops

Homeopathic Remedy

2 FL. OZ. (59 mL)